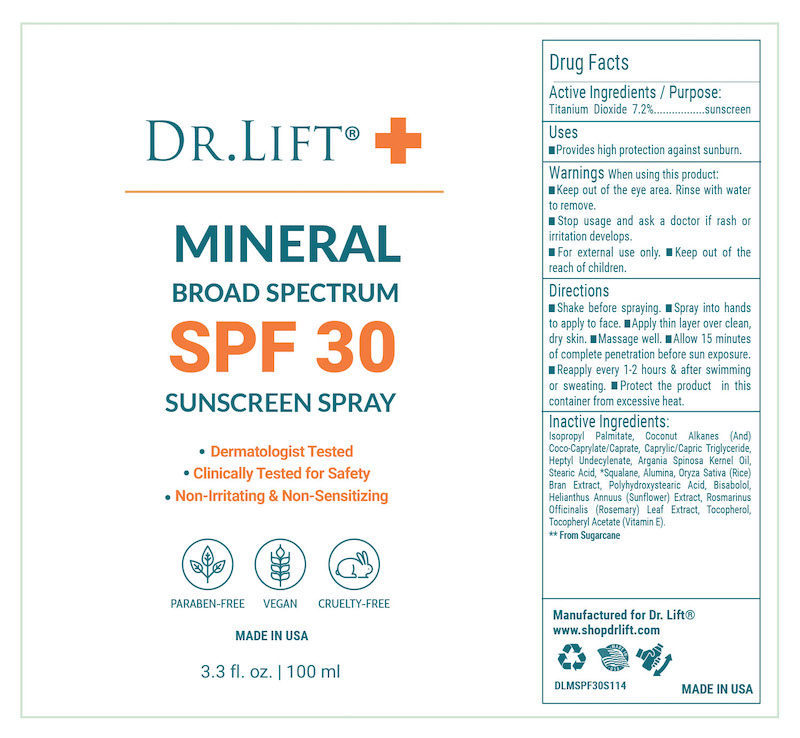 DRUG LABEL: Dr Lift Mineral SPF 30
NDC: 68062-8312 | Form: SPRAY
Manufacturer: Spa de Soleil
Category: otc | Type: HUMAN OTC DRUG LABEL
Date: 20251009

ACTIVE INGREDIENTS: TITANIUM DIOXIDE 72 mg/100 mL
INACTIVE INGREDIENTS: ALUMINA; ORYZA SATIVA (RICE) BRAN; STEARIC ACID; SQUALANE; POLYHYDROXYSTEARIC ACID (2300 MW); HELIANTHUS ANNUUS FLOWERING TOP; PONGAMIA GLABRA SEED OIL; ROSMARINUS OFFICINALIS (ROSEMARY) LEAF OIL; TOCOPHEROL; ALPHA-TOCOPHEROL ACETATE; CARTHAMUS TINCTORIUS (SAFFLOWER) SEED OIL; COCONUT ALKANES; COCO-CAPRYLATE/CAPRATE; CAPRYLIC/CAPRIC TRIGLYCERIDE; HELIANTHUS ANNUUS (SUNFLOWER) SEED OIL; VITIS VINIFERA (GRAPE) SEED OIL; OLEA EUROPAEA (OLIVE) FRUIT OIL; ARGANIA SPINOSA KERNEL OIL; BISABOLOL

Dr Lift Mineral SPF 50

Active Ingredients

Titanium Dioxide 7.2%

Purpose

Sunscreen

Warnings

WarningsWhen using this product

- keep out of the eye area
- rinse with water to remove
- stop use and ask a doctor if rash or irritation develops
- for external use onlyl
- keep out of reach of children

Keep out of reach of children.

Directions

Shake before spraying. Spray into hands to apply to face. Apply thin layer over clean, dry skin. Massage well. Allow 15 minutes of complete penetration before sun exposure. Reapply every 1-2 hours & after swimming or sweating. Protect the product in this container from excessive heat.

Uses
Provides high protection against sunburn.

Inactive Ingredients

Isopropyl Palmitate, Coconut Alkanes (And) Coco-Caprylate/Caprate, Caprylic/Capric Triglyceride, Heptyl Undecylenate, Argania Spinosa Kernel Oil, Stearic Acid, *Squalane, Alumina, Oryza Sativa (Rice) Bran Extract, Polyhydroxystearic Acid, Bisabolol, Helianthus Annuus (Sunflower) Extract, Rosmarinus Officinalis (Rosemary) Leaf Extract, Tocopherol, Tocopheryl Acetate (Vitamin E).